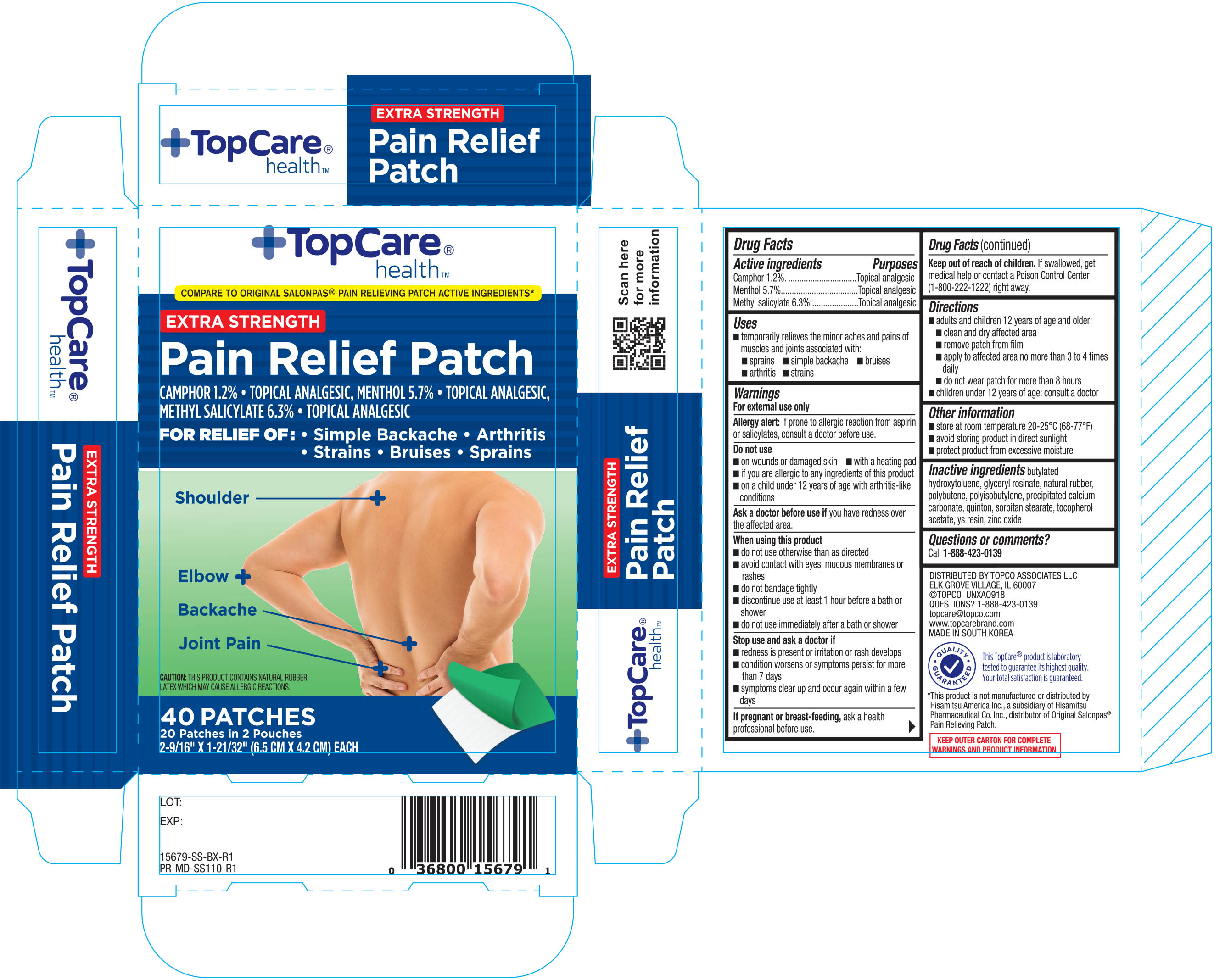 DRUG LABEL: Topcare Pain Relieving 40ct
NDC: 36800-679 | Form: PATCH
Manufacturer: Topco Associates LLC
Category: otc | Type: HUMAN OTC DRUG LABEL
Date: 20221215

ACTIVE INGREDIENTS: CAMPHOR (SYNTHETIC) 0.012 mg/1 g; MENTHOL 0.057 mg/1 g; MENTHYL SALICYLATE, (+/-)- 0.063 mg/1 g
INACTIVE INGREDIENTS: BUTYLATED HYDROXYTOLUENE; GLYCERYL ROSINATE; POLYISOBUTYLENE (1100000 MW); CALCIUM CARBONATE; ZINC OXIDE; NATURAL LATEX RUBBER; POLYBUTENE (1400 MW); SORBITAN MONOSTEARATE; ALPHA-TOCOPHEROL ACETATE

TopCare Pain Relieving Patch 40ct (Small) (15679)

Active ingredients Purpose

Camphor 1.2%....................................................... Topical Analgesic
Menthol 5.7%......................................................... Topical Analgesic

Methyl Salicylate 6.3%............................................. Topical Analgesic

Uses

For temporary relief of minor aches and pains of muscles and joints associated with:

- sprains
- simple backache
- bruises
- arthritis
- strains

Warnings

For external use only

Allergy alert: If prone to allergic reaction from aspirin or slicylates, consult a doctor before use.

Do not use

- on wounds or damaged skin
- with a heating pad
- if you are allergic to any ingredients of this product
- on a child under 12 years of age with arthritis-like conditions

Ask a doctor before use if you have redness over the affected area.

When using this product

- do not use otherwise than directed
- avoid contact with the eyes, mucous membranes or rashes
- do not badnage tightly
- discontinue use at least 1 hour before a bath or shower
- do not use immediately after a bath or shower

Stop use and ask a doctor if

- redness is present or irritation or rash develops
- conditions worsen symptoms persist for more than 7 days
- symptoms clear up and occur again withing a few days

PREGNANCY OR BREAST FEEDING

If pregnant or breast-feeding, ask a health professional before use.

KEEP OUT OF REACH OF CHILDREN

Keep out of the reach of children. If swallowed, get medical help or contact a Poision Control Center (1-800-222-1222) right away.

Directions

adults and children 12 years of age and over:

- clean and dry affected area
- remove patch from film
- apply to affected area not more than 3 to 4 times daily
- do not wear patch for more than 8 hours
- children under 12 years of age: consult a doctor

Other information

- store at room temperature 20-25°C (68-77°F)
- avoid storing product in direct sunlight
- protect product from excessive moisture

INACTIVE INGREDIENT

butylated hydroxytoluene, glyceryl rosinate, natural rubber, polybutene, polyisobutylene, precipitated calcium carbonate, quinton, sorbitan stearate, tocopherol acetate, ys resin, zinc oxide

Questions or comments?

Call 1-888-423-0139

DOSAGE AND ADMINISTRATION

DISTRIBUTED BY:Topco Associates LLC

Elk Grove Village, IL 60007

topcare@topco.com

www.topcarebrand.com

MADE IN SOUTH KOREA